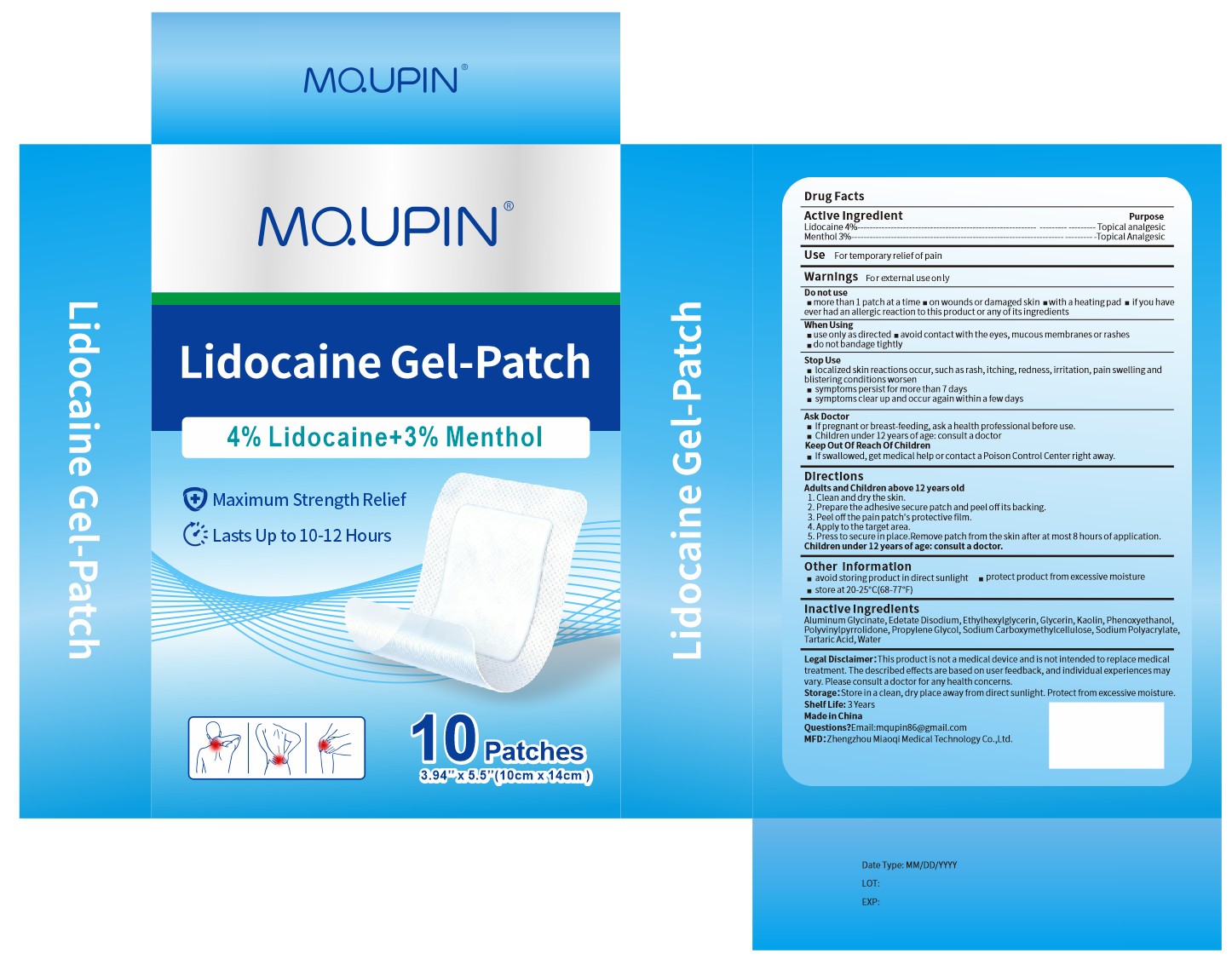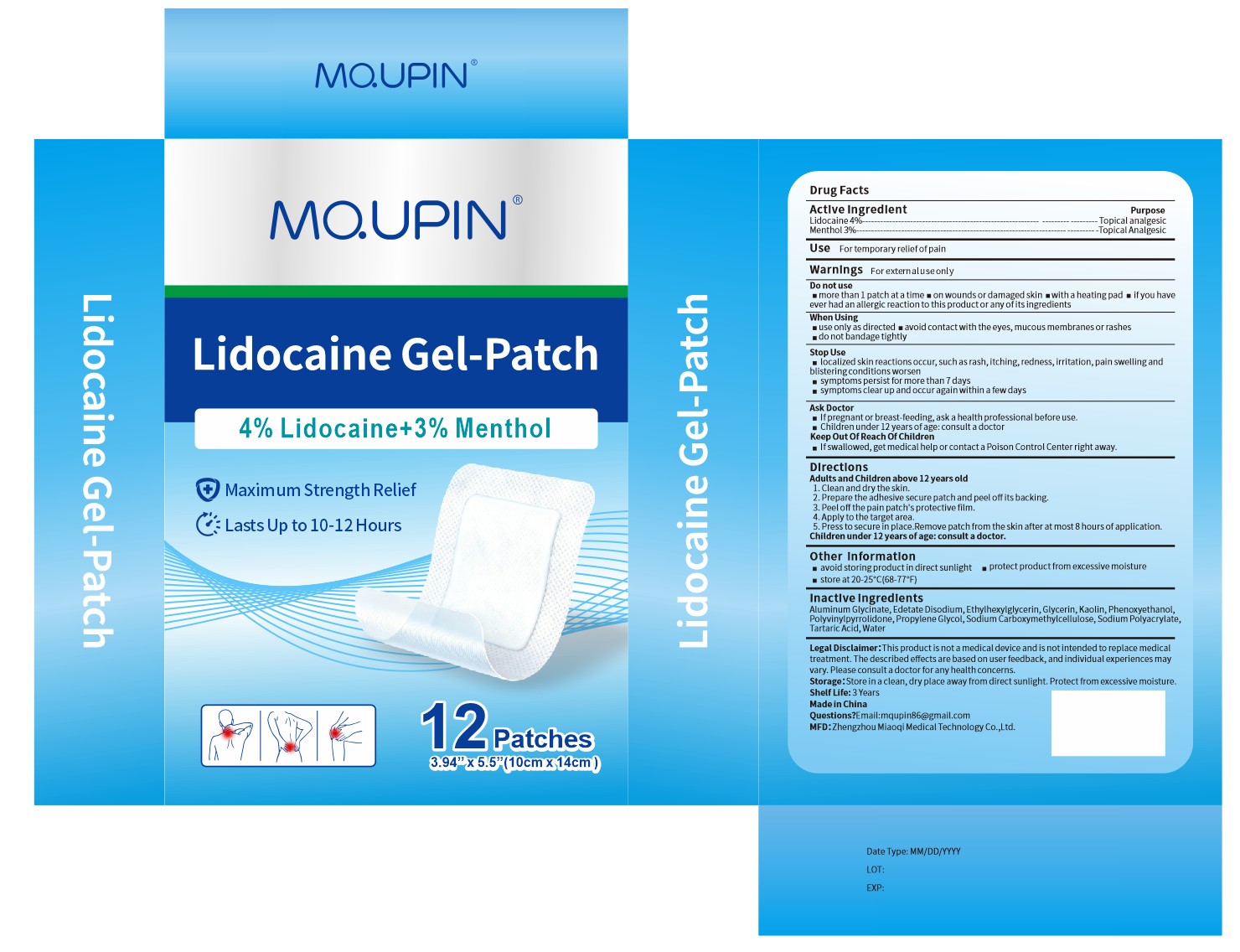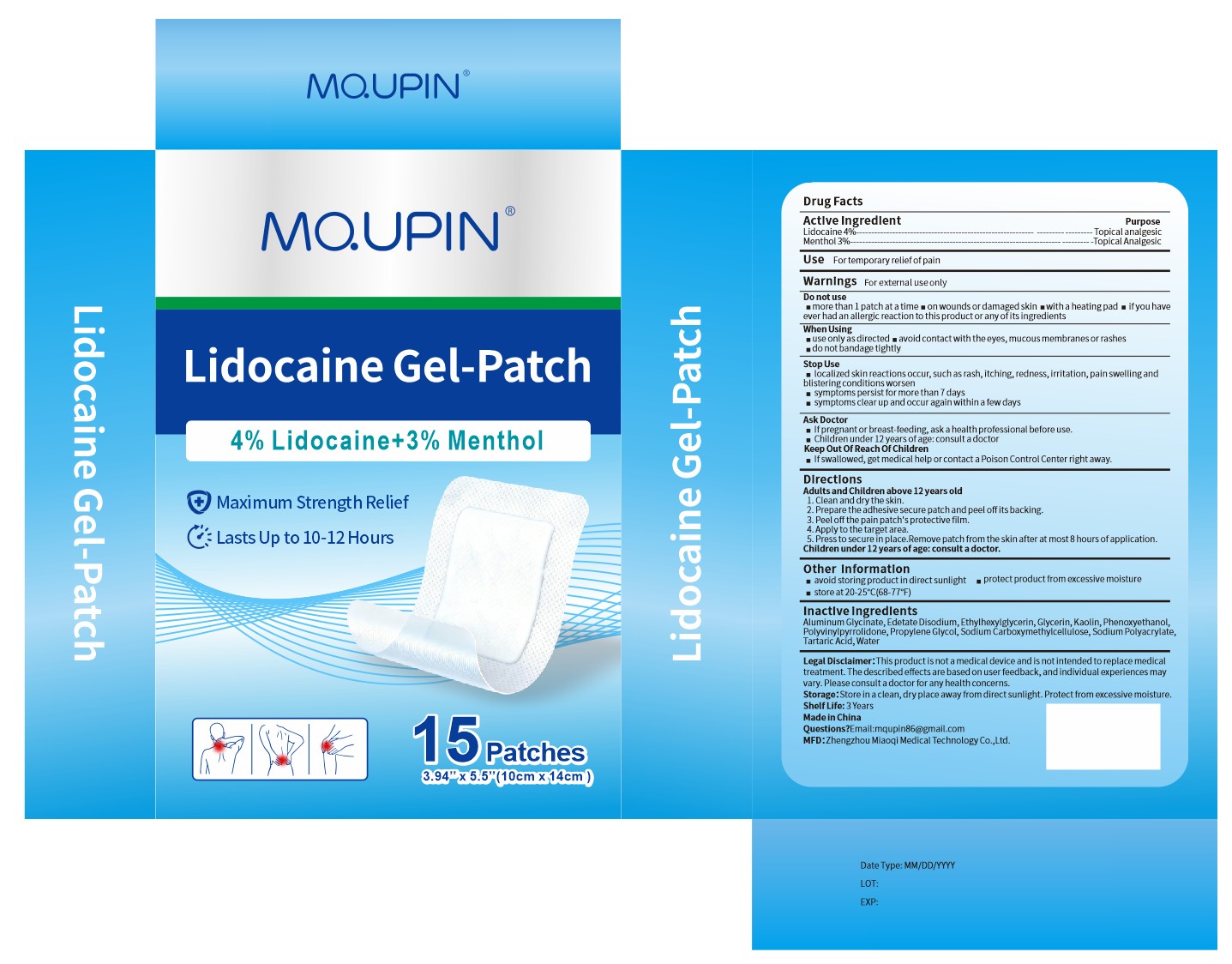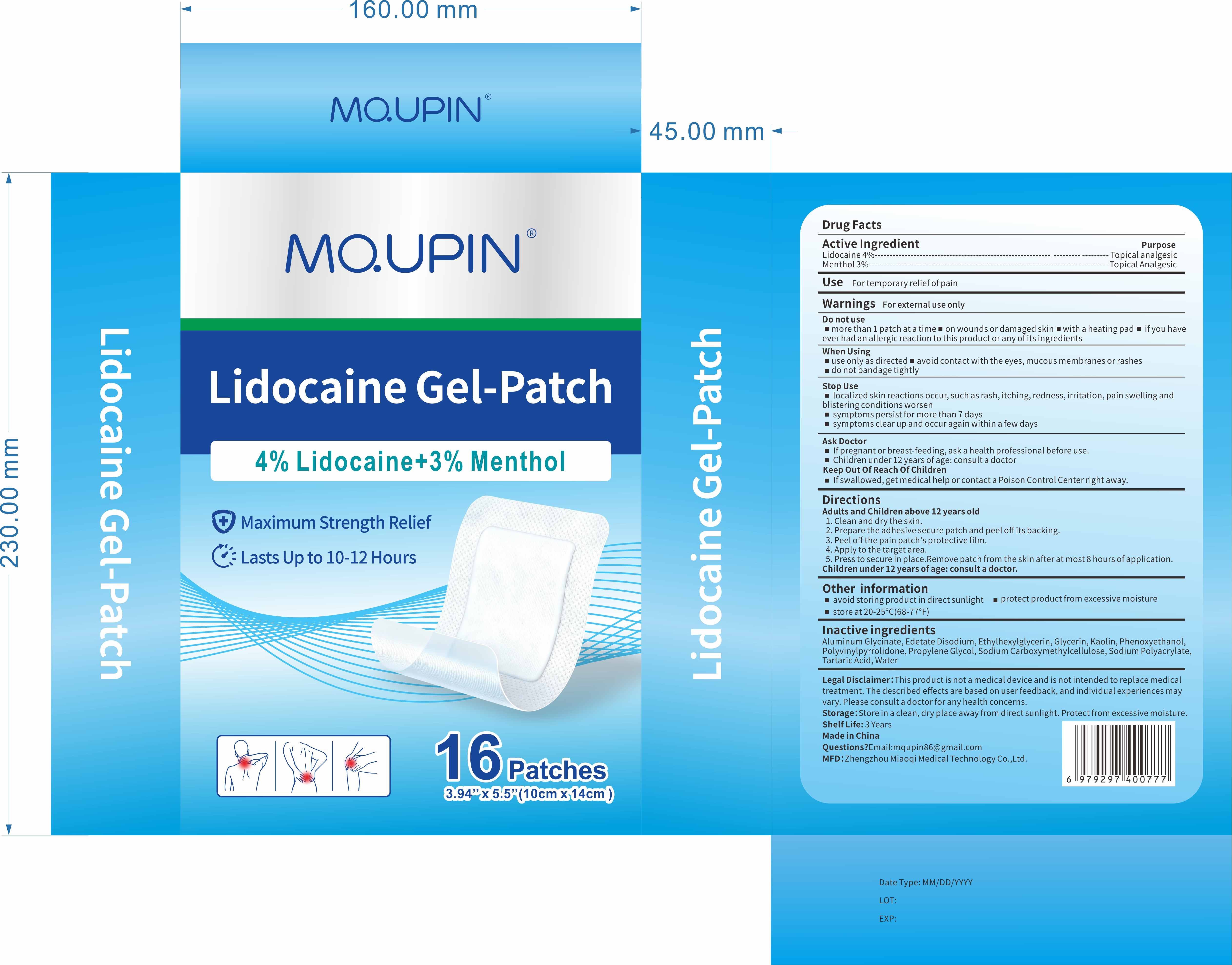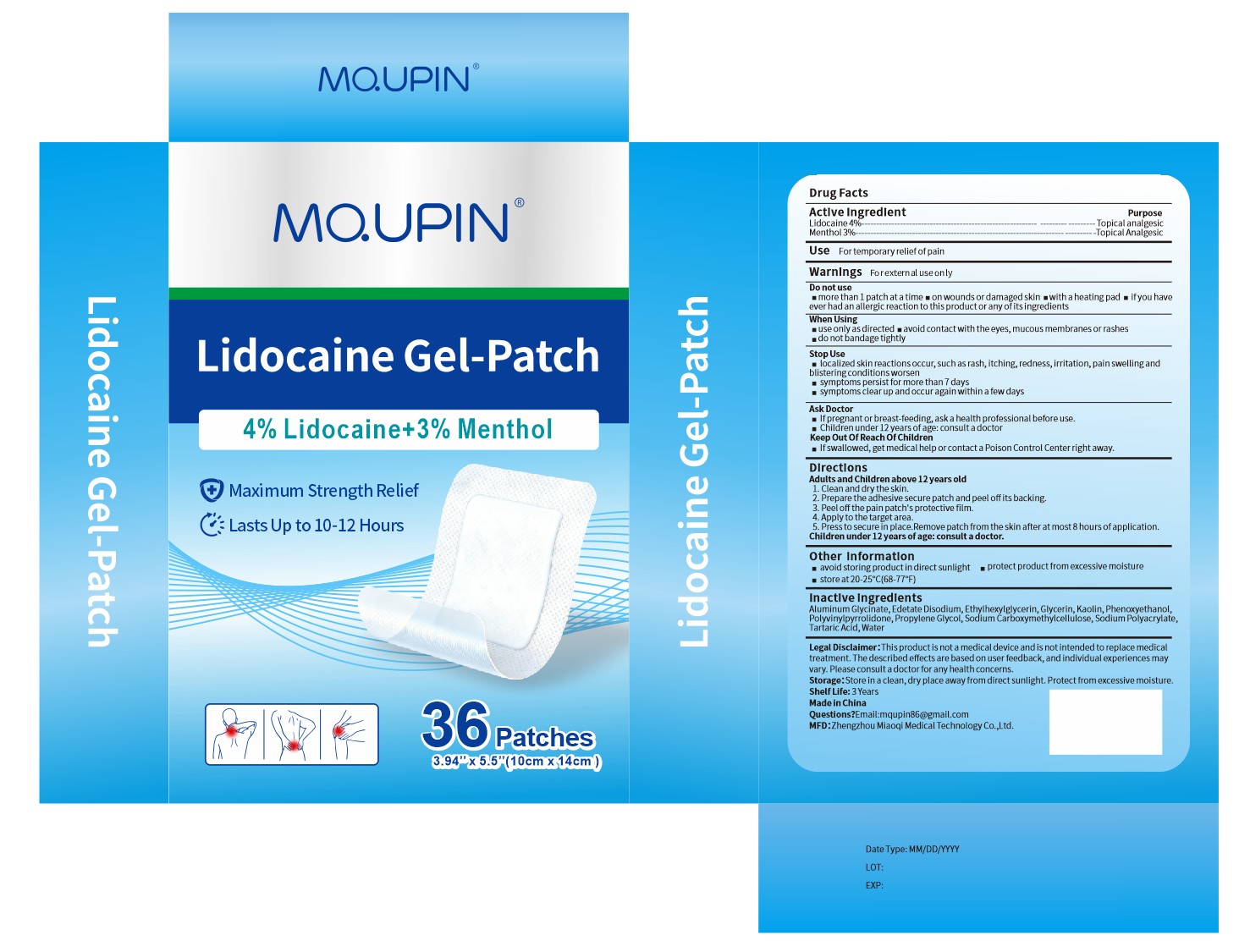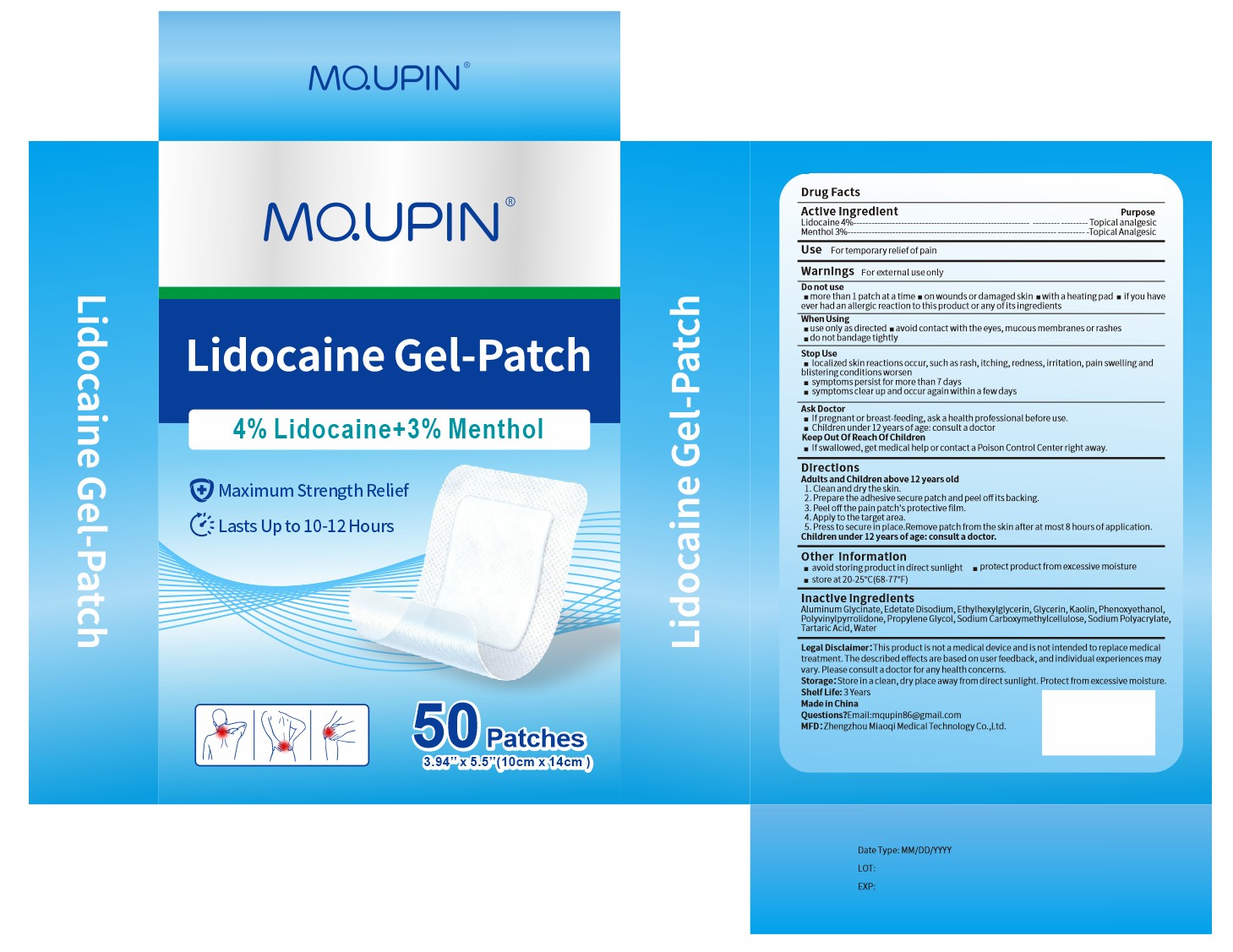 DRUG LABEL: MQUPIN Lidocaine Gel-Patch
NDC: 83781-014 | Form: PATCH
Manufacturer: Zhengzhou Miaoqi Medical Technology Co., Ltd.
Category: otc | Type: HUMAN OTC DRUG LABEL
Date: 20260128

ACTIVE INGREDIENTS: MENTHOL 3 g/100 1; LIDOCAINE 4 g/100 1
INACTIVE INGREDIENTS: PROPYLENE GLYCOL; EDETATE DISODIUM; POLYACRYLIC ACID (250000 MW); DIHYDROXYALUMINUM AMINOACETATE; KAOLIN; METHYLPARABEN; GLYCERIN; POLYSORBATE 80; PROPYLPARABEN; WATER; SODIUM POLYACRYLATE (2500000 MW); POVIDONE K90; TITANIUM DIOXIDE; TARTARIC ACID

83781-014

Active Ingredient

Lidocaine 4%
Menthol 3%

Purpose

Topical Analgesic

Use

For temporary relief of pain

Warnings

For external use only

Do not use

█ more than 1 patch at a time

█ on wounds or damaged skin

█ with a heating pad

█ if you have ever had an allergic reaction to this product or any of its ingredients

When Using

█ use only as directed

█ avoid contact with the eyes, mucous membranes or rashes

█ do not bandage tightly

Stop Use

localized skin reactions occur, such as rash, itching, redness, irritation, pain swelling and blistering conditions worsen

█ symptoms persist for more than 7 days

█ symptoms clear up and occur again within a few days

Ask Doctor

█ If pregnant or breast-feeding, ask a health professional before use.

█ Children under 12 years of age: consult a doctor

Keep Out Of Reach Of Children

If swallowed, get medical help or contact a Poison Control Center right away.

Directions

Adults and Children above 12 years old
1.Clean and dry the skin.
2.Prepare the adhesive secure patch and peel off its backing.
3.Peel off the pain patch's protective film.
4.Apply to the target area.
5.Press to secure in place.Remove patch from the skin after at most 8 hours of application.
Children under 12 years of age: consult a doctor.

Other information

█ avoid storing product in direct sunlight

█ protect product from excessive moisture

█ store at 20-25°C(68-77°F)

Inactive ingredients

Aluminum Glycinate, Edetate Disodium, Ethylhexylglycerin, Glycerin, Kaolin, Phenoxyethanol, Polyvinylpyrrolidone, Propylene Glycol, Sodium Carboxymethylcellulose, Sodium Polyacrylate, Tartaric Acid, Water

Questions

Email:mqupin86@gmail.com